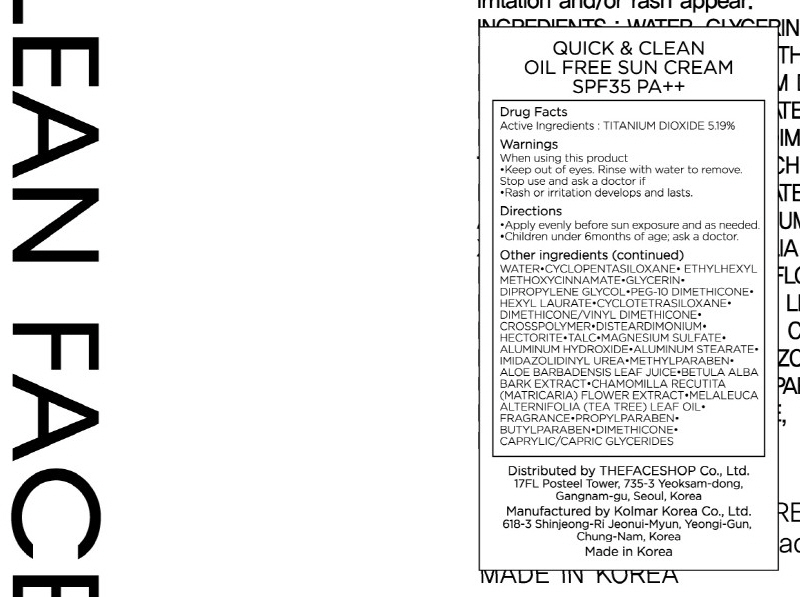 DRUG LABEL: QUICK AND CLEAN OIL FREE SUN
NDC: 51523-003 | Form: CREAM
Manufacturer: THEFACESHOP CO., LTD.
Category: otc | Type: HUMAN OTC DRUG LABEL
Date: 20100712

ACTIVE INGREDIENTS: TITANIUM DIOXIDE 2.59 g/50 g

Drug Facts

Active Ingredient: TITANIUM DIOXIDE

Inactive Ingredients:

WATER, CYCLOPENTASILOXANE, ETHYLHEXYL METHOXYCINNAMATE, GLYCERIN, DIPROPYLENE GLYCOL, PEG-10 DIMETHICONE, HEXYL LAURATE, CYCLOTETRASILOXANE,
DIMETHICONE/VINYL DIMETHICONE, CROSSPOLYMER, DISTEARDIMONIUM, HECTORITE, TALC, MAGNESIUM SULFATE, ALUMINUM HYDROXIDE, ALUMINUM STEARATE,
IMIDAZOLIDINYL UREA, METHYLPARABEN, ALOE BARBADENSIS LEAF JUICE, BETULA ALBA BARK EXTRACT, CHAMOMILLA RECUTITA (MATRICARIA) FLOWER EXTRACT,
MELALEUCA ALTERNIFOLIA (TEA TREE) LEAF OIL, FRAGRANCE, PROPYLPARABEN, BUTYLPARABEN, DIMETHICONE, CAPRYLIC/CAPRIC GLYCERIDES

Warnings:
When using this product
Keep out of eyes. Rinse with water to remove.
Stop use and ask a doctor if
Rash or irritation develops and lasts.
Directions:
Apply evenly before sun exposure and as needed.
Children under 6months of age; ask a doctor.